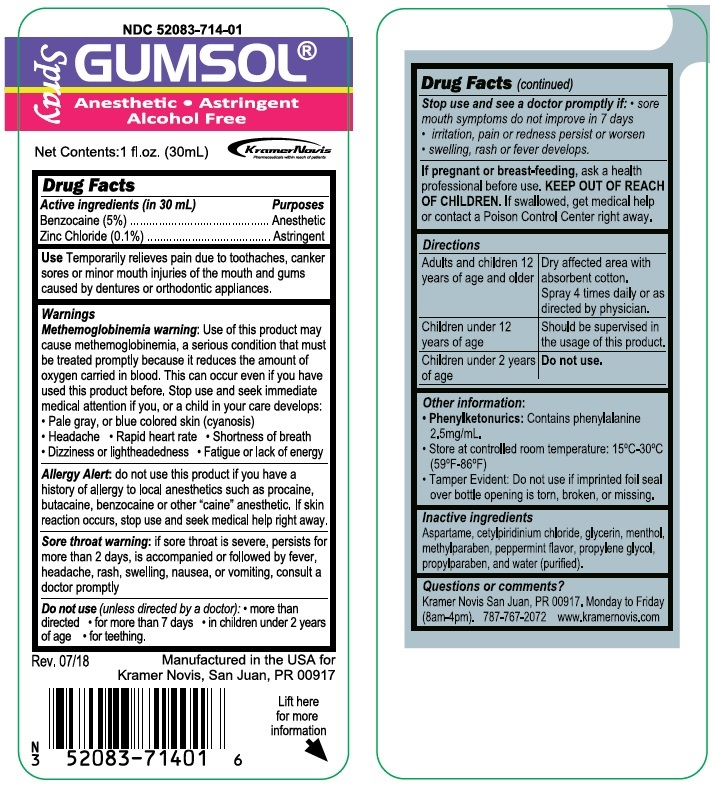 DRUG LABEL: Gumsol
                        
NDC: 52083-714 | Form: SPRAY
Manufacturer: Kramer Novis
Category: otc | Type: HUMAN OTC DRUG LABEL
Date: 20251115

ACTIVE INGREDIENTS: BENZOCAINE 1.5 g/30 mL; ZINC CHLORIDE 0.03 g/30 mL
INACTIVE INGREDIENTS: ASPARTAME; CETYLPYRIDINIUM CHLORIDE; GLYCERIN; MENTHOL, UNSPECIFIED FORM; METHYLPARABEN; PROPYLENE GLYCOL; PROPYLPARABEN; WATER

GUMSOL

Active ingredients (in 30 mL)

Benzocaine (5%)

Zinc Chloride (0.1%)

Purposes

Anesthetic

Astringent

Use

Temporarily relieves pain due to toothaches, canker sores or minor mouth injuries of the mouth and gums caused by dentures or orthodontic appliances.

Warnings

Methemoglobinemia warning: Use of this product may cause methemoglobinemia, a serious condition that must be treated promptly because it reduces the amount of oxygen carried in blood. This can occur even if you have used this product before. Stop use and seek immediate medical attention if you, or a child in your care develops:

• Pale gray, or blue colored skin (cyanosis)

• Headache • Rapid heart rate • Shortness of breath

• Dizziness or lightheadedness • Fatigue or lack of energy

Allergy Alert: do not use this product if you have a history of allergy to local anesthetics such as procaine, butacaine, benzocaine or other "caine" anesthetic. If skin reaction occurs, stop use and seek medical help right away.

Sore throat warning: if sore throat is severe, persists for more than 2 days, is accompanied or followed by fever, headache, rash, swelling, nausea, or vomiting, consult a doctor promptly

Do not use (unless directed by a doctor): • more than directed • for more than 7 days • in children under 2 years of age • for teething.

Stop use and see a doctor promptly if: • sore mouth symptoms do not improve in 7 days

• irritation, pain or redness persist or worsen

• swelling, rash or fever develops.

If pregnant or breast-feeding, ask a health professional before use.

KEEP OUT OF REACH OF CHILDREN. If swallowed, get medical help or contact a Poison Control Center right away.

Directions

Adults and children 12 years of age and older | Dry affected area with absorbent cotton.; Spray 4 times daily or as directed by physician.
Children under 12 years of age | Should be supervised in the usage of this product.
Children under 2 years of age | Do not use.

Other information:

• Phenylketonurics: Contains phenylalanine 2.5mg/mL.

• Store at controlled room temperature: 15°C-30°C (59°F-86°F)

• Tamper Evident: Do not use if imprinted foil seal over bottle opening is torn, broken, or missing.

Inactive ingredients

Aspartame, cetylpyridinium chloride, glycerin, menthol, methylparaben, peppermint flavor, propylene glycol, propylparaben, and water (purified).

Questions or comments?

Kramer Novis San Juan, PR 00917. Monday to Friday

(8am-4pm). 787-767-2072 www.kramernovis.com

Spray

Alcohol Free

Manufactured in the USA for

Kramer Novis, San Juan, PR 00917